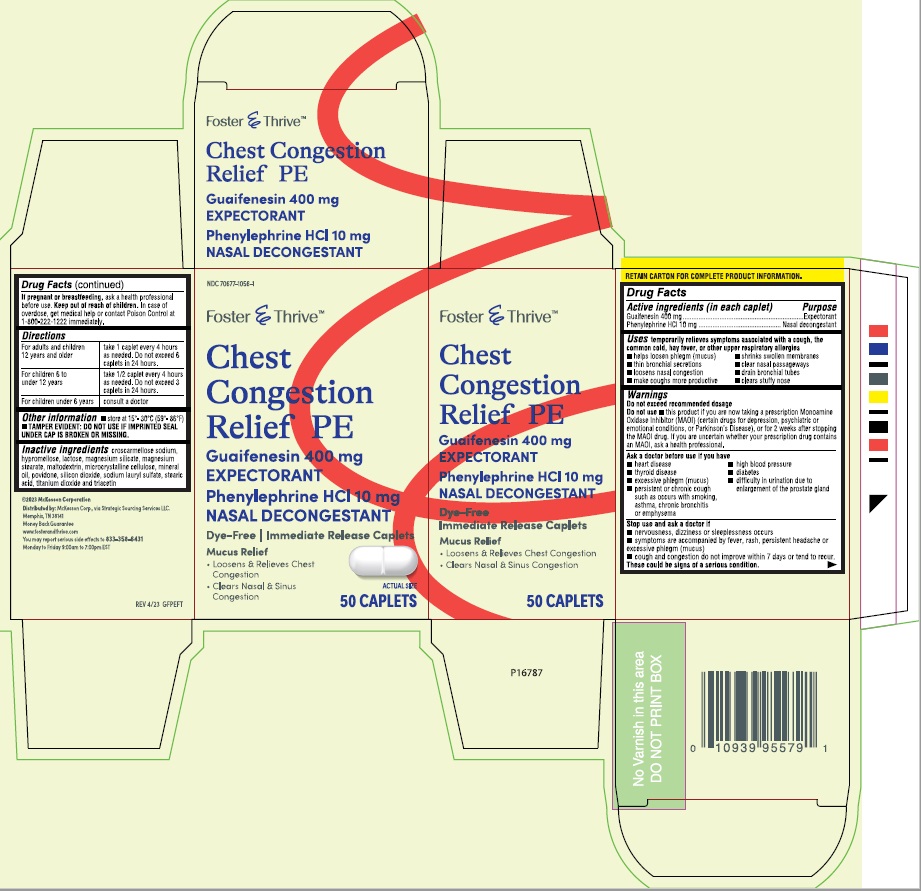 DRUG LABEL: Foster and Thrive Chest Congestion Relief PE
NDC: 70677-1056 | Form: TABLET
Manufacturer: Strategic Sourcing Services LLC
Category: otc | Type: HUMAN OTC DRUG LABEL
Date: 20260115

ACTIVE INGREDIENTS: Guaifenesin 400 mg/1 1; PHENYLEPHRINE HYDROCHLORIDE 10 mg/1 1
INACTIVE INGREDIENTS: CROSCARMELLOSE SODIUM; LACTOSE; MALTODEXTRIN; CELLULOSE, MICROCRYSTALLINE; MINERAL OIL; POVIDONE; MAGNESIUM SILICATE; MAGNESIUM STEARATE

DRUG FACTS

Active ingredient - (per tablet)

Guaifenesin 400 mg
Phenylephrine HCl 10 mg

Purpose

Guaifenesin.......................Expectorant
Phenylephrine HCl..............Nasal decongestant

Uses

Temporarily relieves symptoms associated with a cough ,the common cold,hay fever or other upper respiratory allergies.
■ helps loosen phlegm (mucus)
■ clear nasal passageways
■ loosens nasal congestion
■ drain bronchial tubes
■ shrinks swollen membranes
■ clears stuffy nose
■ makes coughs more productive

Warnings

Do not exceed recommended dosage

Do not use

■ this product if you are now taking a prescription monoamine oxidase inhibitor (MAOI) (certain drugs for depression,
psychiatric or emotional conditions, or Parkinson’s Disease), or for 2 weeks after stopping the
MAOI drug. If you are uncertain whether your prescription drug contains an MAOI, ask a health
professional.

Ask a doctor before use if you have

■ heart disease
■ high blood pressure
■ thyroid disease
■ diabetes
■ excessive phlegm;mucus
■ difficulty in urination due to an enlarged prostate gland
■ persistent or chronic cough such as occurs with smoking,asthma,chronic bronchitis or emphysema

Stop use and ask a doctor if

■ nervousness, dizziness or sleeplessness occurs
■ symptoms are accompanied by fever, rash,
persistent headache or excessive phlegm (mucus)
■ cough and congestion do not improve within 7 days
or tend to recur.
These could be signs of a serious condition.

If pregnant or breast-feeding, ask a health
professional before use.

KEEP OUT OF REACH OF CHILDREN

Keep out of the reach of children. In case of overdose, get medical help or contact a Poison
Control Center immediately.

Directions

■ adults and children 12 years and over:
take 1 caplet every 4 hours as needed
■ children 6 to under 12 years:
take 1/2 caplet every 4 hours as needed
■ children under 6 years: consult a doctor
Do not exceed 6 doses in a 24 hour period or as directed by a doctor.

Inactive ingredients

lactose, magnesium silicate,
croscarmellose sodium, hypromellose, magnesium stearate, maltodextrin,
microcrystalline cellulose, mineral oil, povidone, silica, sodium lauryl sulfate, stearic acid,
titanium dioxide and triacetin